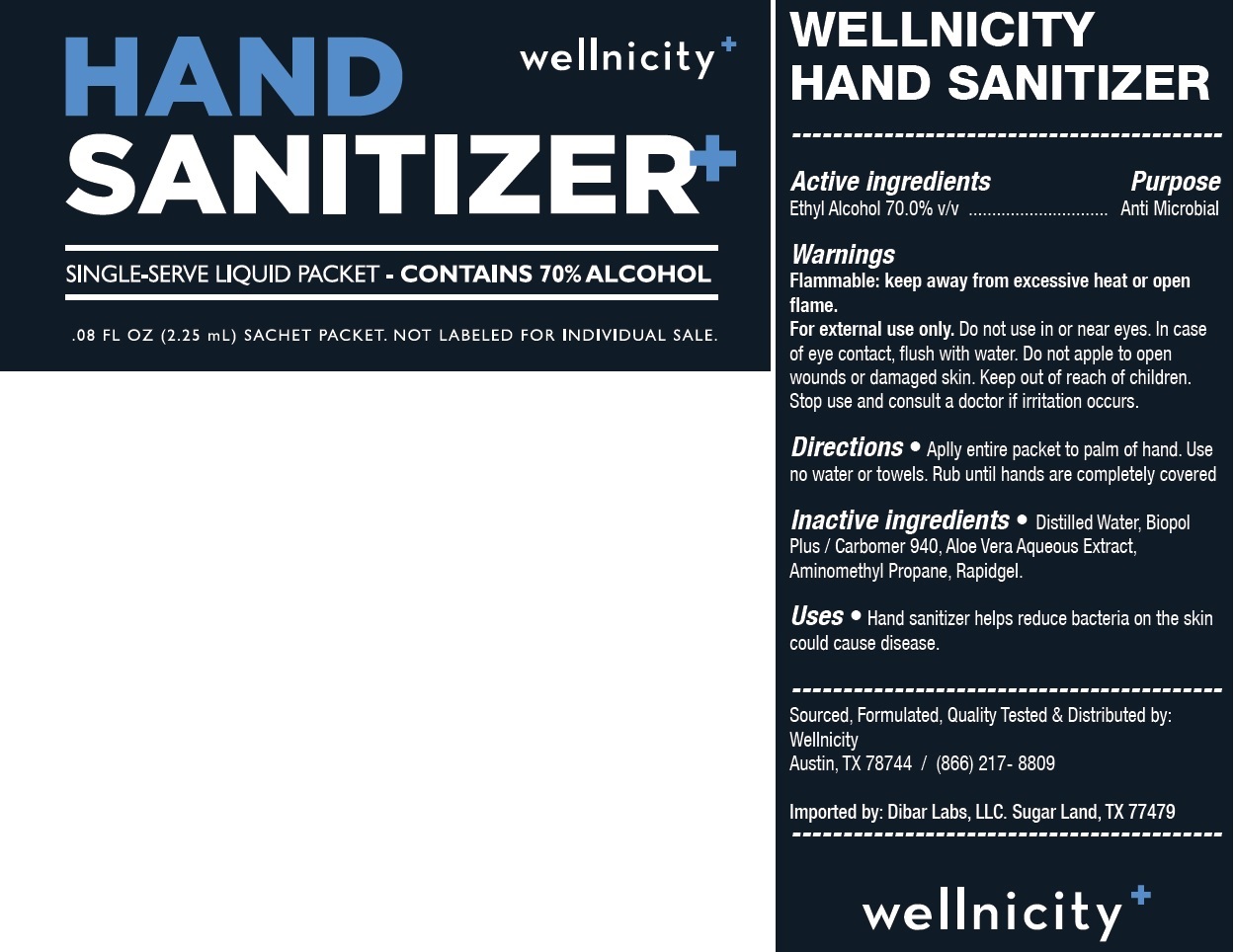 DRUG LABEL: Wellnicity Hand Sanitizer
NDC: 62400-0017 | Form: GEL
Manufacturer: United Laboratories Manufacturing, LLC
Category: otc | Type: HUMAN OTC DRUG LABEL
Date: 20200730

ACTIVE INGREDIENTS: ALCOHOL 0.7 mL/1 mL
INACTIVE INGREDIENTS: WATER; CARBOMER HOMOPOLYMER TYPE C (ALLYL PENTAERYTHRITOL CROSSLINKED); ALOE VERA LEAF; AMINOMETHYL PROPANEDIOL; RAPIDGEL EZ1

Wellnicity Hand Sanitizer

Active ingredients

Ethyl Alcohol 70.0% v/v

Purpose

Anti Microbial

Warnings

Flammable: keep away from excessive heat or open flame.

For external use only.

Do not use

in or near eyes. In case of eye contact, flush with water. Do not apple to open wounds or damaged skin.

Stop use and consult a doctor

if irritation occurs.

Directions

- Aplly entire packet to palm of hand. Use no water or towels. Rub until hands are completely covered.

Inactive ingredients

Distilled Water, Biopol Plus / Carbomer 940, Aloe Vera Aqueous Extract, Aminomethyl Propane, Rapidgel.

Uses

- Hand sanitizer helps reduce bacteria on the skin could cause disease.

Product Label

C:\Users\RegCorp 142\Downloads\Download SPL\Listings to submit to FDA\United Laboratories Manufacturing, LLC (73009-017) Wellnicity Hand Sanitizer